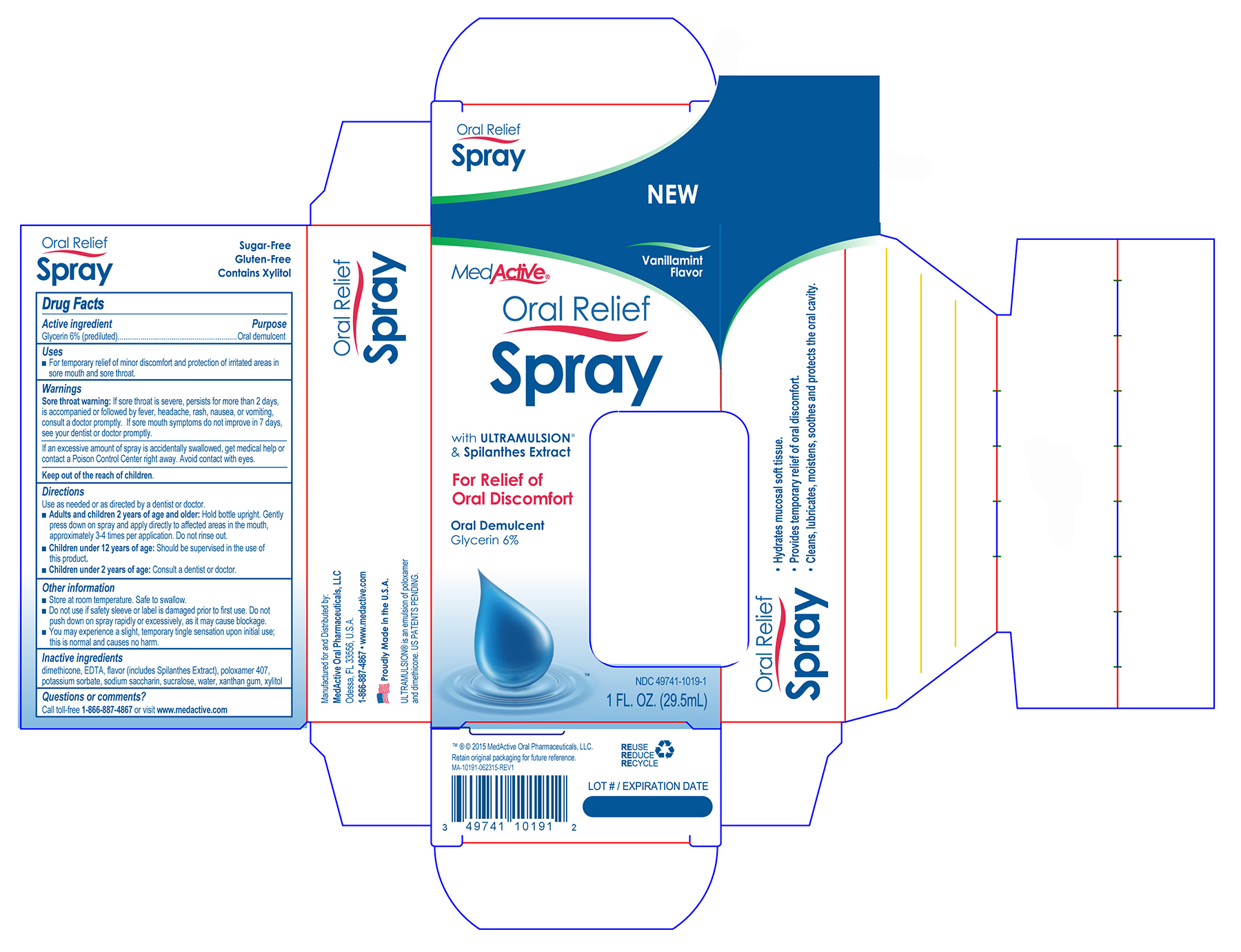 DRUG LABEL: MedActive Oral Relief
NDC: 49741-1019 | Form: SPRAY
Manufacturer: Integrate Oral Care, LLC.
Category: otc | Type: HUMAN OTC DRUG LABEL
Date: 20211230

ACTIVE INGREDIENTS: GLYCERIN 29.5 mg/1 mL
INACTIVE INGREDIENTS: WATER 1 mg/1 mL; XYLITOL 1 mg/1 mL; DIMETHICONE 1 mg/1 mL; EDETIC ACID 1 mg/1 mL; POLOXAMER 407 1 mg/1 mL; POTASSIUM SORBATE 1 mg/1 mL; SUCRALOSE 1 mg/1 mL; SACCHARIN SODIUM 1 mg/1 mL; XANTHAN GUM 1 mCi/1 mL

Active Ingredient

Glycerin 6% (prediluted)

Purpose

Oral Demulcent

Uses

For temporary relief of minor discomfort and protection of irritated areas in sore mouth and sore throat.

Warnings

Sore Throat warning: If sore throat is severe, persists for more than 2 days, is accompanied or followed by fever, headache, rash, nausea, or vomiting, consult a doctor promptly. If sore mouth symptoms do not improve in 7 days, see your dentist or doctor promptly.

If an excessive amount of spray is accidentally swwallowed, get medical help or contact a Poison Control Center right away. Avoid contact with eyes.

Keep out of the reach of children.

Directions

Use as needed or as directed by a dentist or doctor.

- Adults and children 2 years or age and older: Hold bottle upright. Gently press down on spray and apply directly to affected areas in the mouth, approximately 3-4 times per application. Do not rinse out.
- Children under 12 years of age: Should be supervised in the use of this product.
- Children under 2 years of age: Consult a dentist or doctor.

Other Information

- Store at room temperature. Safe to swallow.
- Do not use if safety sleeve or label is damaged prior to first use. Do not push down on spray rapidly or excessively, as it may cause blockage.
- You may experience a slight, temporary tingle sensation upon initial use; this is normal and cuases no harm.

Inactive Ingredients

dimethicone, EDTA, flavor (includes Spilanthes Extract), poloxamer 407, potassium sorbate, sodium saccharin, sucralose, water, xanthan gum, xylitol

Questions or comments?

Call toll-free 1-866-887-4867 or visit www.integrateoralcare.com

PACKAGE LABEL

NEW Vanillamint Flavor

MedActive® Oral Relief Spray

with ULTRAMULSION® & Spilanthes Extract

For Relief of Oral Discomfort

Oral Demulcent

Glycerin 6%

NDC 49741-101901

1 FL. OZ. (29.5mL)